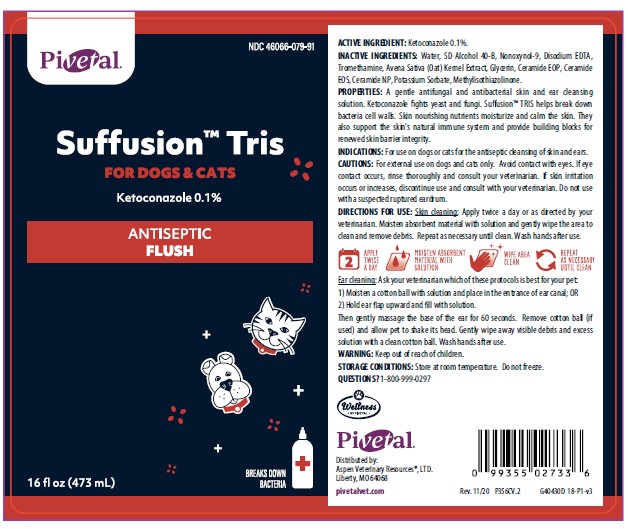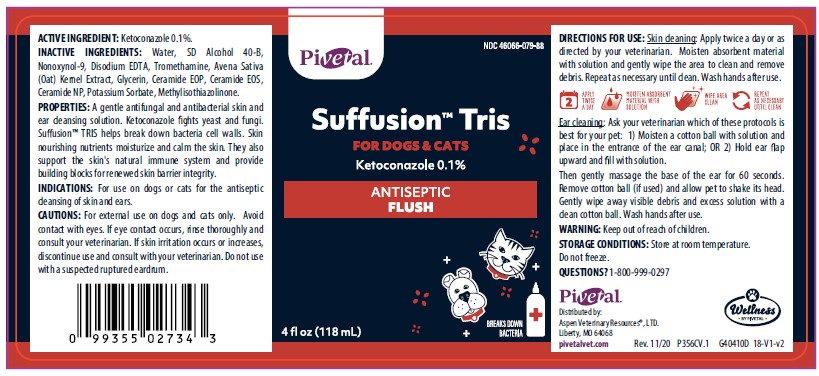 DRUG LABEL: Suffusion
NDC: 46066-079 | Form: SOLUTION
Manufacturer: ASPEN VETERINARY RESOURCES
Category: animal | Type: OTC ANIMAL DRUG LABEL
Date: 20210402

ACTIVE INGREDIENTS: KETOCONAZOLE 1 mg/1 mL
INACTIVE INGREDIENTS: WATER; ALCOHOL; NONOXYNOL-9; EDETATE DISODIUM; TROMETHAMINE; AVENANTHRAMIDES; GLYCERIN; CERAMIDE 1; CERAMIDE EOS; CERAMIDE NP; POTASSIUM SORBATE; METHYLISOTHIAZOLINONE

DESCRIPTION

Suffusion™ TRIS

FOR DOGS AND CATS

Ketoconazole 0.1%

ANTISEPTIC FLUSH

ACTIVE INGREDIENTS: Ketoconazole 0.1%.

INACTIVE INGREDIENTS: Water, SD Alcohol 40-B, Nonoxynol-9, Disodium EDTA, Tromethamine, Avena Sativa (Oat) Kernal Extract, Glycerin, Ceramide EOP, Ceramide EOS, Ceramide NP, Potassium Sorbate, Methylisothiazolinone.

PROPERTIES: A gentle antifungal and antibacterial skin and ear cleansing solution. Ketoconazole fights yeast and fungi. TRIS helps break down bacteria cell walls. Skin nourishing nutrients moisturize and calm the skin. They also support the skin's natural immune system and provide building blocks for renewed skin barrier integrity.

INDICATIONS AND USAGE

INDICATIONS: For use on dogs or cats for the antiseptic cleansing of skin and ears.

DIRECTIONS FOR USE: Skin Cleaning: Apply twice a day or as directed by your veterinarian. Moisten absorbent material with solution and gently wipe the area to clean and remove debris. Repeat as necessary until clean. Wash hands after use.

Ear Cleaning: Ask your veterinarian which of these protocols is best for your pet. 1) Moisten a cotton ball with solution and place in entrance of ear canal; OR 2) Hold the ear flap upwards and fill the ear canal with solution.

Then, gently massage the base of the ear for 60 seconds. Remove cotton ball (if used) and allow pet to shake its head. Gently wipe away debris and excess solution with a clean, dry cotton ball. Wash hands after use.

PRECAUTIONS

CAUTIONS: For external use on dogs and cats only. Avoid contact with the eyes. If eye contact occurs, rinse thoroughly and consult your veterinarian. If skin irritation occurs or increases, discontinue use and consult with your veterinarian. Do not use in the case of a suspected ruptured eardrum.

WARNING: Keep out of reach of children.

STORAGE AND HANDLING

STORAGE CONDITIONS: Store at room temperature. Do not freeze.

QUESTIONS? 1-800-999-0297

Pivetal

Distributed by:

Aspen Veterinary Resources®, LTD.

Liberty, MO 64068

pivetalvet.com

PRINCIPAL DISPLAY PANEL - 4 OUNCE (118 mL) Bottle

Pivetal

NDC 46066-079-88

Suffusion™ TRIS

FOR DOGS AND CATS

Ketoconazole 0.1%

ANTISEPTIC FLUSH

4 fl oz (118 mL)

PRINCIPAL DISPLAY PANEL - 16 OUNCE (473 mL) Bottle

Pivetal

NDC 46066-079-91

Suffusion™ TRIS

FOR DOGS AND CATS

Ketoconazole 0.1%

ANTISEPTIC FLUSH

16 fl oz (473 mL)